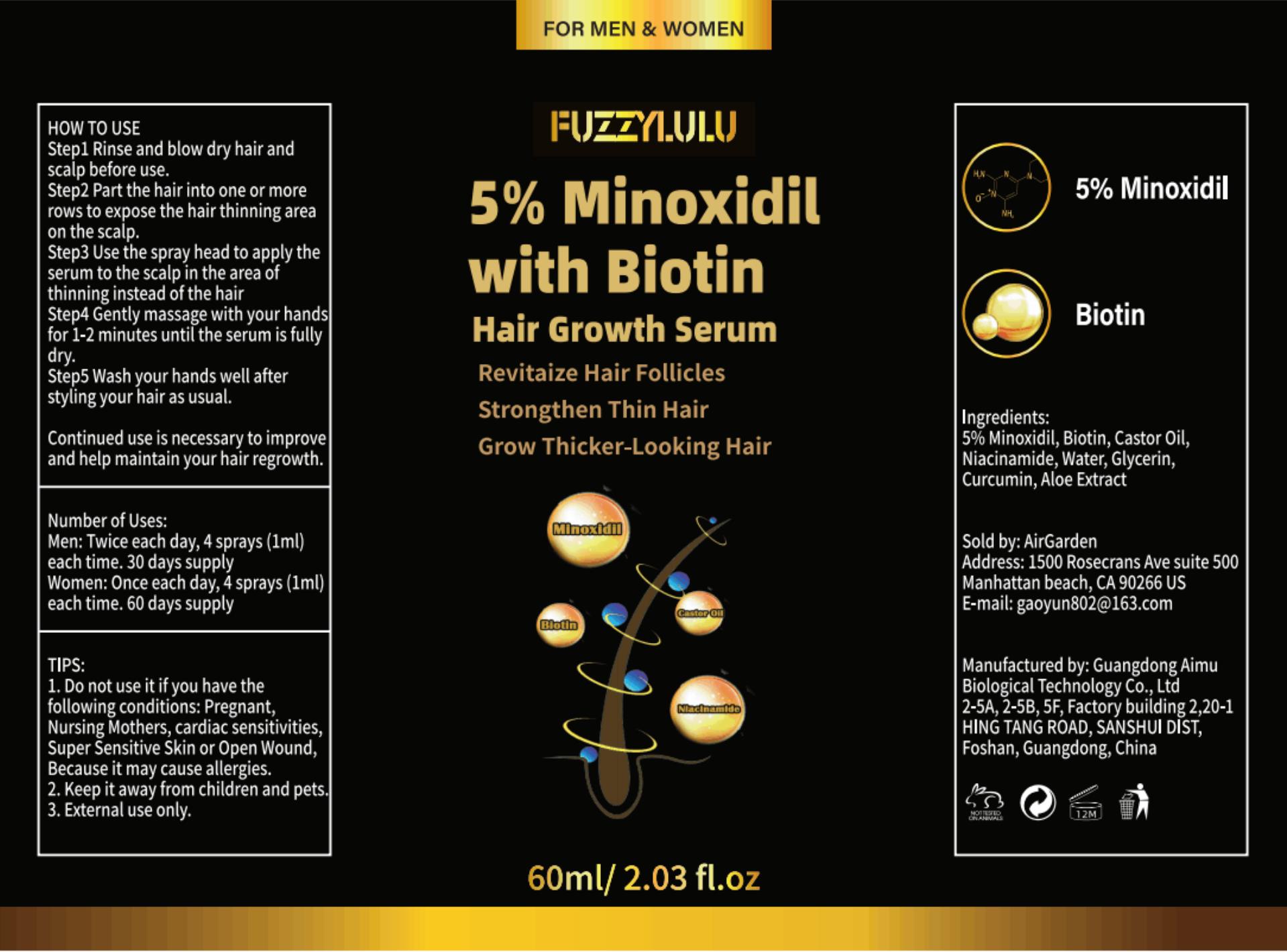 DRUG LABEL: FUZZYLULU 5% Minoxidil with Biotin Hair Growth serum
NDC: 83566-701 | Form: LIQUID
Manufacturer: Guangdong Aimu Biological Technology Co., Ltd
Category: otc | Type: HUMAN OTC DRUG LABEL
Date: 20240514

ACTIVE INGREDIENTS: MINOXIDIL 3 g/60 mL
INACTIVE INGREDIENTS: GLYCERIN; CURCUMIN; WATER; NIACINAMIDE; BIOTIN; CASTOR OIL; ALOE

FUZZYLULU 5% Minoxidil with Biotin Hair Growth serum

ACTIVE INGREDIENT

MINOXIDIL 5%

PURPOSE

Revitaize Hair Follicles
Strongthen Thin Hair
Grow Thicker-Looking Hair

Keep it away from children and pets

INDICATIONS AND USAGE

HOW TO USE
Step1 Rinse and blow dry hair andscalp before use.
Step2 Part the hair into one or morerows to expose the hair thinning areaon the scalp.
Step3 Use the spray head to apply theserum to the scalp in the area ofthinning instead of the hair
Step4 Gently massage with your handsfor 1-2 minutes until the serum is fullydry.
Step5 Wash your hands well afterstyling your hair as usual.
Continued use is necessary to improveand help maintain your hair regrowth.

WARNINGS

External use only.

DOSAGE AND ADMINISTRATION

Number of Uses:
Men: Twice each day, 4 sprays (1ml)each time. 30 days supply
Women: Once each day, 4 sprays (1ml)each time. 60 days supply

STORAGE AND HANDLING

Store in a cool place

INACTIVE INGREDIENT

Biotinyl
Castor Oil
Niacinamide
Water
Glycerin
Curcumin
Aloe Extract